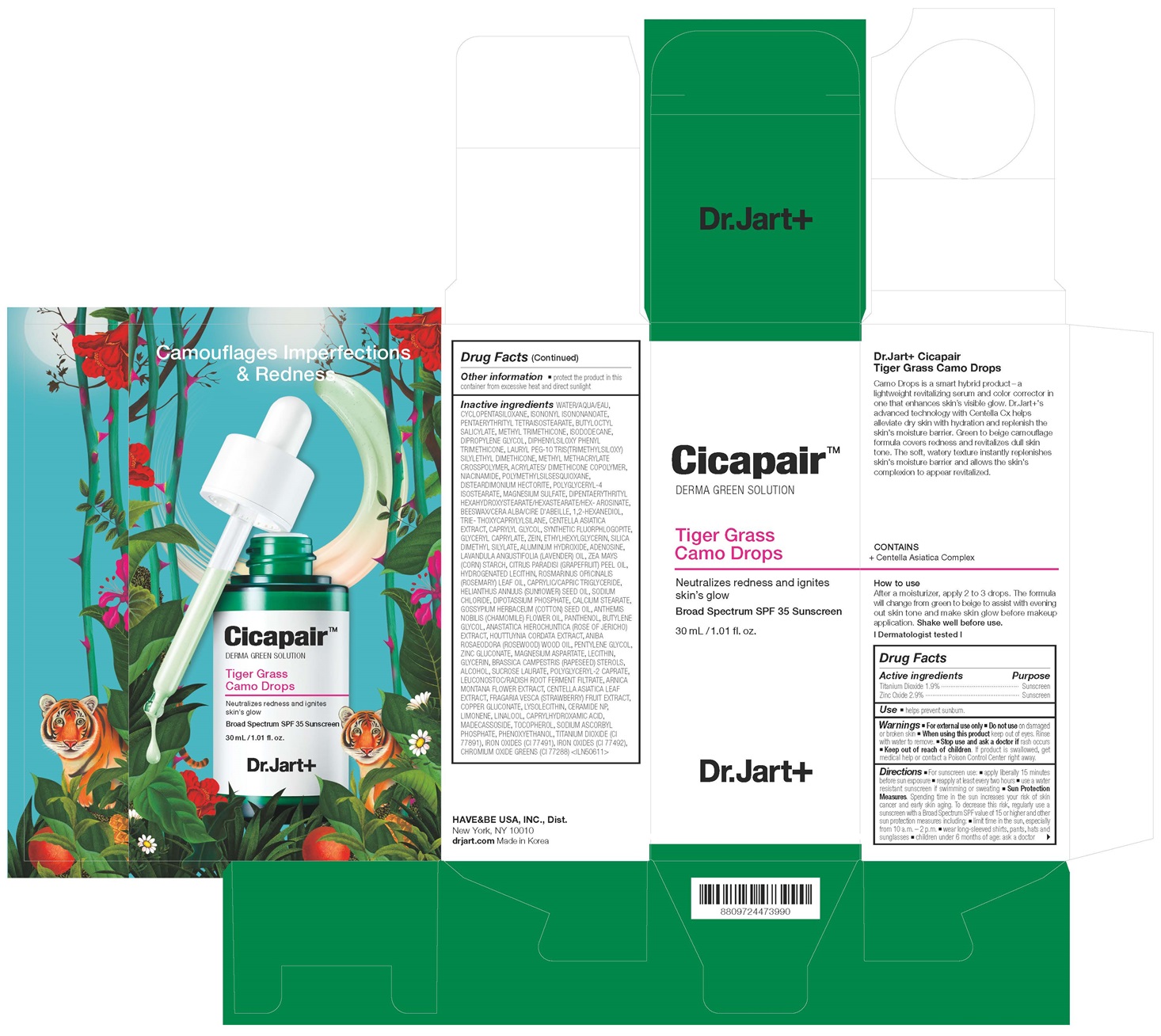 DRUG LABEL: DR.JART CICAPAIR TIGER GRASS CAMO DROPS
NDC: 49404-152 | Form: CREAM
Manufacturer: Have & Be Co., Ltd.
Category: otc | Type: HUMAN OTC DRUG LABEL
Date: 20241225

ACTIVE INGREDIENTS: ZINC OXIDE 29 mg/1 mL; TITANIUM DIOXIDE 19 mg/1 mL
INACTIVE INGREDIENTS: DIPENTAERYTHRITYL HEXAHYDROXYSTEARATE; COPPER GLUCONATE; LINALOOL, (+/-)-; TOCOPHEROL; ALCOHOL; FERRIC OXIDE RED; WATER; CYCLOMETHICONE 5; METHYL TRIMETHICONE; POLY(METHYL METHACRYLATE; 450000 MW); NIACINAMIDE; POLYMETHYLSILSESQUIOXANE (4.5 MICRONS); TRIETHOXYCAPRYLYLSILANE; CENTELLA ASIATICA TRITERPENOIDS; SILICA DIMETHYL SILYLATE; LAVENDER OIL; GRAPEFRUIT OIL; ROSEMARY OIL; SUNFLOWER OIL; CHAMAEMELUM NOBILE FLOWER OIL; LECITHIN, SOYBEAN; RAPESEED STEROL; SUCROSE LAURATE; LEUCONOSTOC/RADISH ROOT FERMENT FILTRATE; ARNICA MONTANA FLOWER; CERAMIDE NP; PHENOXYETHANOL; ISODODECANE; DIPHENYLSILOXY PHENYL TRIMETHICONE; CETYL DIGLYCERYL TRIS(TRIMETHYLSILOXY)SILYLETHYL DIMETHICONE (3500 MM2/S); DISTEARDIMONIUM HECTORITE; MAGNESIUM SULFATE, UNSPECIFIED; 1,2-HEXANEDIOL; CAPRYLYL GLYCOL; ETHYLHEXYLGLYCERIN; ALUMINUM HYDROXIDE; ADENOSINE; SODIUM CHLORIDE; POTASSIUM PHOSPHATE, DIBASIC; LEVANT COTTON OIL; ZINC GLUCONATE; ISONONYL ISONONANOATE; DIPROPYLENE GLYCOL; POLYGLYCERYL-4 ISOSTEARATE; YELLOW WAX; PENTYLENE GLYCOL; GLYCERIN; CENTELLA ASIATICA LEAF; LIMONENE, (+)-; CAPRYLHYDROXAMIC ACID; PANTHENOL; BUTYLENE GLYCOL; ROSEWOOD OIL; MAGNESIUM ASPARTATE; LYSOPHOSPHATIDYLCHOLINE, SOYBEAN; MADECASSOSIDE; SODIUM ASCORBYL PHOSPHATE; PENTAERYTHRITYL TETRAISOSTEARATE; BUTYLOCTYL SALICYLATE; 2-ETHYLHEXYL ACRYLATE, METHACRYLATE, METHYL METHACRYLATE, OR BUTYL METHACRYLATE/HYDROXYPROPYL DIMETHICONE COPOLYMER (30000-300000 MW); MAGNESIUM POTASSIUM ALUMINOSILICATE FLUORIDE; GLYCERYL CAPRYLATE; STARCH, CORN; MEDIUM-CHAIN TRIGLYCERIDES; ZEIN; ANASTATICA HIEROCHUNTICA WHOLE; HOUTTUYNIA CORDATA FLOWERING TOP; POLYGLYCERYL-2 CAPRATE; FRAGARIA VESCA FRUIT; HYDROGENATED SOYBEAN LECITHIN; CALCIUM STEARATE; FERRIC OXIDE YELLOW; CHROMIC OXIDE

[NEW] Dr.Jart Cicapair Tiger Grass Camo Drops

Active ingredients

Titanium Dioxide 1.9%

Zinc Oxide 2.9%

Purpose

Sunscreen

Use

helps prevent sunburn.

Warnings

For external use only

Do not use

on damaged or broken skin

When using this product

keep out of eyes. Rinse with water to remove

Stop use and ask a doctor if

rash occurs

Keep out of reach of children.

If product is swallowed, get medical help or contact a Poison Control Center right away

Directions

■ For sunscreen use: ■ apply liberally 15 minutes
before sun exposure ■ reapply at least every two hours ■ use a water
resistant sunscreen if swimming or sweating ■ Sun Protection
Measures. Spending time in the sun increases your risk of skin
cancer and early skin aging. To decrease this risk, regularly use a
sunscreen with a Broad Spectrum SPF value of 15 or higher and other
sun protection measures including: ■ limit time in the sun, especially
from 10 a.m. – 2 p.m. ■ wear long-sleeved shirts, pants, hats and
sunglasses ■ children under 6 months of age: ask a doctor

Inactive ingredients

WATER/AQUA/EAU,
CYCLOPENTASILOXANE, ISONONYL ISONONANOATE,
PENTAERYTHRITYL TETRAISOSTEARATE, BUTYLOCTYL
SALICYLATE, METHYL TRIMETHICONE, ISODODECANE,
DIPROPYLENE GLYCOL, DIPHENYLSILOXY PHENYL
TRIMETHICONE, LAURYL PEG-10 TRIS(TRIMETHYLSILOXY)
SILYLETHYL DIMETHICONE, METHYL METHACRYLATE
CROSSPOLYMER, ACRYLATES/ DIMETHICONE COPOLYMER,
NIACINAMIDE, POLYMETHYLSILSESQUIOXANE,
DISTEARDIMONIUM HECTORITE, POLYGLYCERYL-4
ISOSTEARATE, MAGNESIUM SULFATE, DIPENTAERYTHRITYL
HEXAHYDROXYSTEARATE/HEXASTEARATE/HEX- AROSINATE,
BEESWAX/CERA ALBA/CIRE D'ABEILLE, 1,2-HEXANEDIOL,
TRIE- THOXYCAPRYLYLSILANE, CENTELLA ASIATICA
EXTRACT, CAPRYLYL GLYCOL, SYNTHETIC FLUORPHLOGOPITE,
GLYCERYL CAPRYLATE, ZEIN, ETHYLHEXYLGLYCERIN, SILICA
DIMETHYL SILYLATE, ALUMINUM HYDROXIDE, ADENOSINE,
LAVANDULA ANGUSTIFOLIA (LAVENDER) OIL, ZEA MAYS
(CORN) STARCH, CITRUS PARADISI (GRAPEFRUIT) PEEL OIL,
HYDROGENATED LECITHIN, ROSMARINUS OFfiCINALIS
(ROSEMARY) LEAF OIL, CAPRYLIC/CAPRIC TRIGLYCERIDE,
HELIANTHUS ANNUUS (SUNflOWER) SEED OIL, SODIUM
CHLORIDE, DIPOTASSIUM PHOSPHATE, CALCIUM STEARATE,
GOSSYPIUM HERBACEUM (COTTON) SEED OIL, ANTHEMIS
NOBILIS (CHAMOMILE) FLOWER OIL, PANTHENOL, BUTYLENE
GLYCOL, ANASTATICA HIEROCHUNTICA (ROSE OF JERICHO)
EXTRACT, HOUTTUYNIA CORDATA EXTRACT, ANIBA
ROSAEODORA (ROSEWOOD) WOOD OIL, PENTYLENE GLYCOL,
ZINC GLUCONATE, MAGNESIUM ASPARTATE, LECITHIN,
GLYCERIN, BRASSICA CAMPESTRIS (RAPESEED) STEROLS,
ALCOHOL, SUCROSE LAURATE, POLYGLYCERYL-2 CAPRATE,
LEUCONOSTOC/RADISH ROOT FERMENT FILTRATE, ARNICA
MONTANA FLOWER EXTRACT, CENTELLA ASIATICA LEAF
EXTRACT, FRAGARIA VESCA (STRAWBERRY) FRUIT EXTRACT,
COPPER GLUCONATE, LYSOLECITHIN, CERAMIDE NP,
LIMONENE, LINALOOL, CAPRYLHYDROXAMIC ACID,
MADECASSOSIDE, TOCOPHEROL, SODIUM ASCORBYL
PHOSPHATE, PHENOXYETHANOL, TITANIUM DIOXIDE (CI
77891), IRON OXIDES (CI 77491), IRON OXIDES (CI 77492),
CHROMIUM OXIDE GREENS (CI 77288) <ILN50611>

Other information

■ protect the product in this
container from excessive heat and direct sunlight

PRINCIPAL DISPLAY PANEL

Cicapair

DERMA GREEN SOLUTION

Tiger Grass Camo Drops

Neutralizes redness and ignites
skin’s glow

Broad Spectrum SPF 35 Sunscreen

30 mL / 1.01 fl. oz.

Dr.Jart+